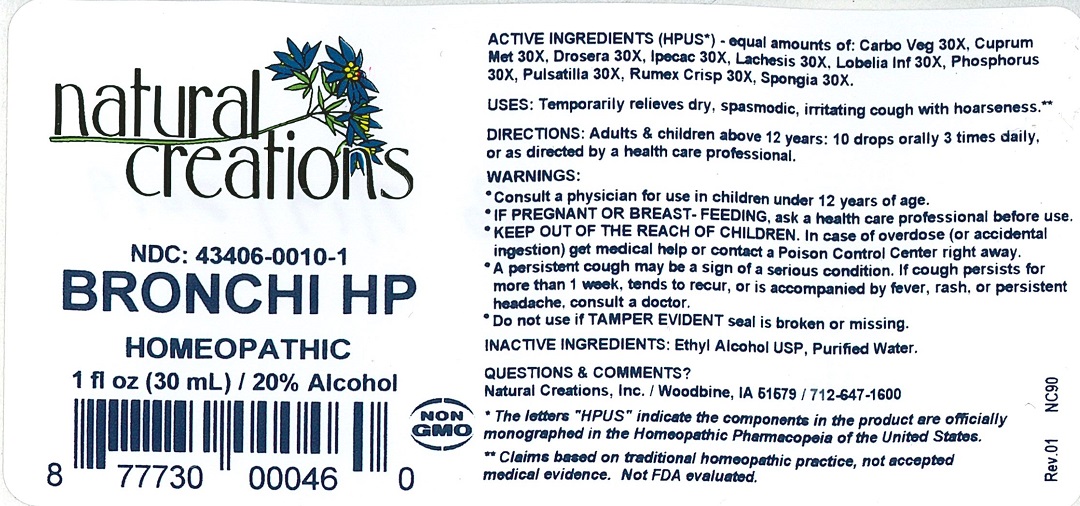 DRUG LABEL: Bronchi HP
NDC: 43406-0010 | Form: LIQUID
Manufacturer: Natural Creations, Inc.
Category: homeopathic | Type: HUMAN OTC DRUG LABEL
Date: 20251113

ACTIVE INGREDIENTS: ACTIVATED CHARCOAL 30 [hp_X]/1 mL; COPPER 30 [hp_X]/1 mL; DROSERA ROTUNDIFOLIA 30 [hp_X]/1 mL; IPECAC 30 [hp_X]/1 mL; LACHESIS MUTA VENOM 30 [hp_X]/1 mL; LOBELIA INFLATA 30 [hp_X]/1 mL; PHOSPHORUS 30 [hp_X]/1 mL; PULSATILLA VULGARIS 30 [hp_X]/1 mL; RUMEX CRISPUS ROOT 30 [hp_X]/1 mL; SPONGIA OFFICINALIS SKELETON, ROASTED 30 [hp_X]/1 mL
INACTIVE INGREDIENTS: WATER; ALCOHOL

BRONCHI HP

ACTIVE INGREDIENT

ACTIVE INGREDIENTS (HPUS*) - equal amounts of: Carbo Vegetabilis 30X, Cuprum Metallicum 30X, Drosera Rotundifolia 30X, Ipecacuanha 30X, Lachesis Mutus 30X, Lobelia Inflata 30X, Phosphorus 30X, Rumex Crispus 30X, Spongia Tosta 30X

INDICATIONS AND USAGE

USES: Temporarily relieves dry, spasmodic, irritating cough with hoarseness.**

WARNING:

- Consult a physician for use in children under 12 years of age.
- IF PREGNANT OR BREAST-FEEDING, ask a health care professional before use.
- KEEP OUT OF THE REACH OF CHILDREN. In case of overdose (or accidental ingestion) get medical help or contact a Poison Control Center right away.
- If cough persists for more than 1 week, tends to recur, or is accompanied by fever, rash, or persistent headache, consult a doctor.
- Do not use if TAMPER EVIDENT seal is broken or missing.

DOSAGE AND ADMINISTRATION

DIRECTIONS: Adults and children above 12 years: 10 drops orally 3 times daily, or as directed by a health care professional.

REFERENCES

*The letters "HPUS" indicate the components in the product are officially monographed in the Homeopathic Pharmacopeia of the United States.

**Claims based on traditional homeopathic practice, not accepted medical evidence. Not FDA evaluated.

INACTIVE INGREDIENTS: Ethyl Alcohol USP, Purified Water.

QUESTIONS AND COMMENTS?
Natural Creations / Woodbine, IA / 51579 712-647-1600

PURPOSE

USES: Temporarily relieves dry, spasmodic, irritating cough with hoarseness.**

KEEP OUT OF REACH OF CHILDREN

KEEP OUT OF THE REACH OF CHILDREN. In case of overdose (or accidental ingestion) get medical help or contact a Poison Control Center.

PACKAGE LABEL

NDC: 43406-0010-1

BRONCHI HP

HOMEOPATHIC

1 fl oz (30 mL) / 20% Alcohol

UPC: 877730000460